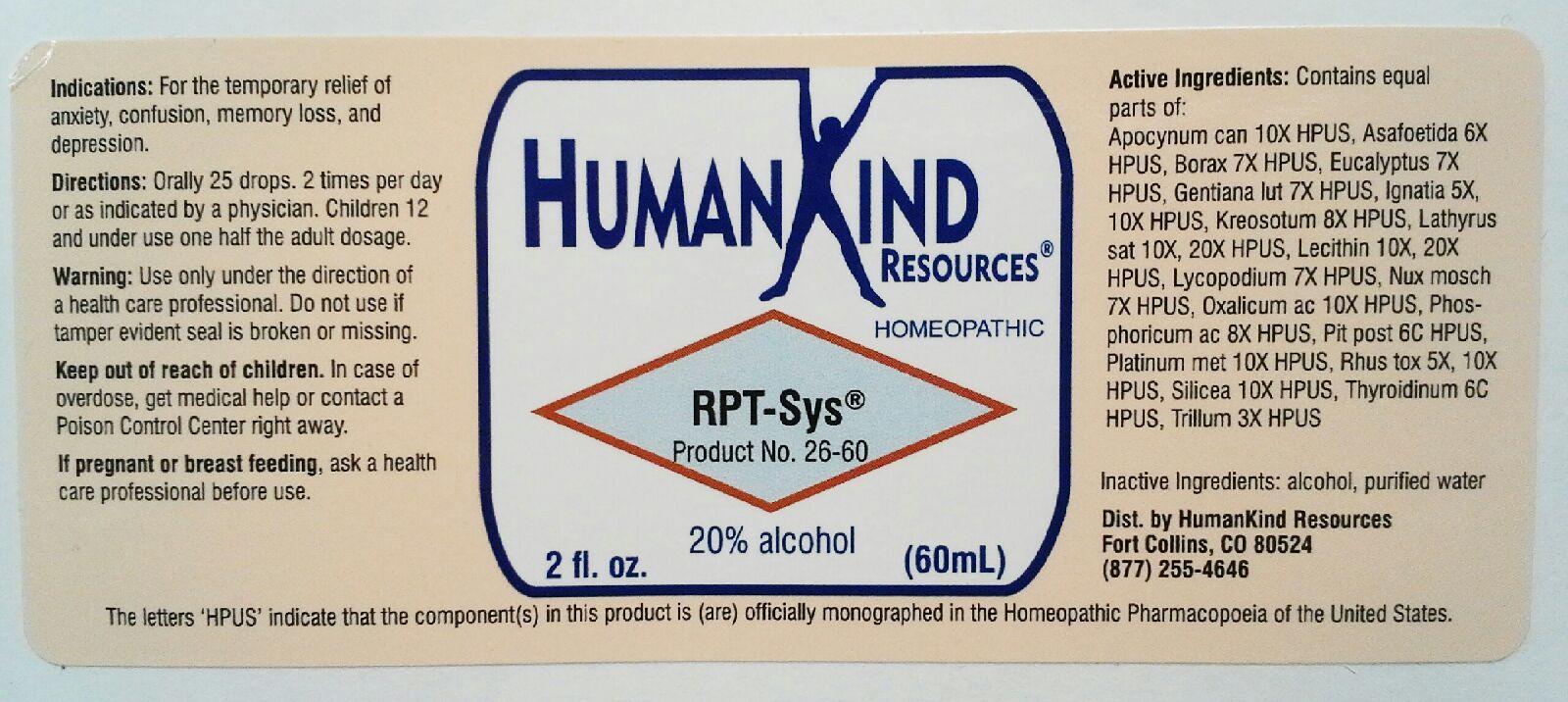 DRUG LABEL: RPT-Sys
NDC: 64616-104 | Form: LIQUID
Manufacturer: Vitality Works, Inc.
Category: homeopathic | Type: HUMAN OTC DRUG LABEL
Date: 20251217

ACTIVE INGREDIENTS: TOXICODENDRON PUBESCENS LEAF 10 [hp_X]/1 mL; SILICON DIOXIDE 10 [hp_X]/1 mL; THYROID, UNSPECIFIED 6 [hp_C]/1 mL; TRILLIUM ERECTUM ROOT 3 [hp_X]/1 mL; APOCYNUM CANNABINUM ROOT 10 [hp_X]/1 mL; ASAFETIDA 6 [hp_X]/1 mL; SODIUM BORATE 7 [hp_X]/1 mL; EUCALYPTUS GLOBULUS LEAF 7 [hp_X]/1 mL; GENTIANA LUTEA ROOT 7 [hp_X]/1 mL; STRYCHNOS IGNATII SEED 10 [hp_X]/1 mL; WOOD CREOSOTE 8 [hp_X]/1 mL; LATHYRUS SATIVAS SEED 20 [hp_X]/1 mL; EGG PHOSPHOLIPIDS 20 [hp_X]/1 mL; LYCOPODIUM CLAVATUM SPORE 7 [hp_X]/1 mL; NUTMEG 7 [hp_X]/1 mL; OXALIC ACID DIHYDRATE 10 [hp_X]/1 mL; PHOSPHORIC ACID 8 [hp_X]/1 mL; SUS SCROFA PITUITARY GLAND 6 [hp_C]/1 mL; PLATINUM 10 [hp_X]/1 mL
INACTIVE INGREDIENTS: ALCOHOL; WATER

RPT-Sys

RPT-Sys

Apocynum Cannabinum 10X Lathyrus Sativus 10X, 20X Plantinum Metallicum 10X

Asafoetida 6X Lecithin 10X, 20X Rhus Toxicodendron 5X, 10X

Borax 7X Lycopodium Clavatum 7X Silicea 10X

Eucalyptus Globulus 7X Nux Moschata 7X Thyroidinum 6C

Gentiana Lutea 7X Oxalicum Acidum 10X Trillum Pendulum 3X

Ignatia Amara 5X, 10X Phophoricum Acidum 8X

Kreosotum 8X Pituitarum Posterium 6C

RPT-Sys

Alcohol, Purified Water

RPT-Sys

Use only under the direction of a health care professional. Do not use if tamper evident seal is broken or missing.

RPT-Sys

Keep out of reach of children. In case of overdose, get medical help or contact a Poison Control Center right away.

RPT-Sys

For the temporary relief of anxiety, confusion, memory loss, and depression.

RPT-Sys

Orally 25 drops, 2 times per day or an indicated by a physician. Children 12 and under use one half the adult dosage.

RPT-Sys

Focuses on the vibrational and electrical balances to the body.